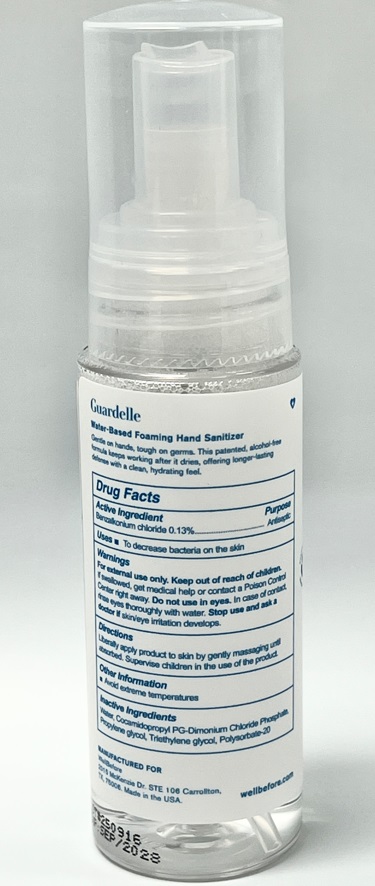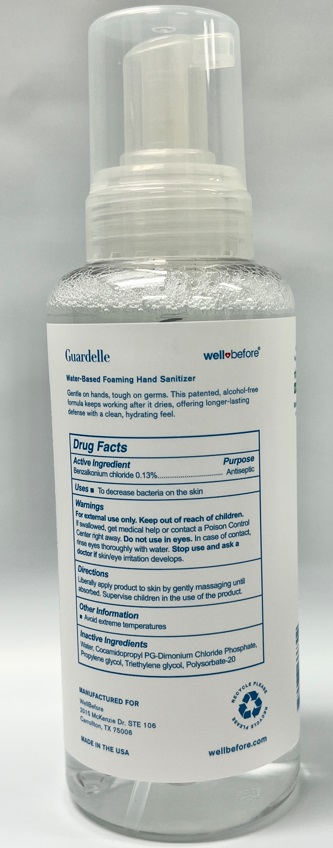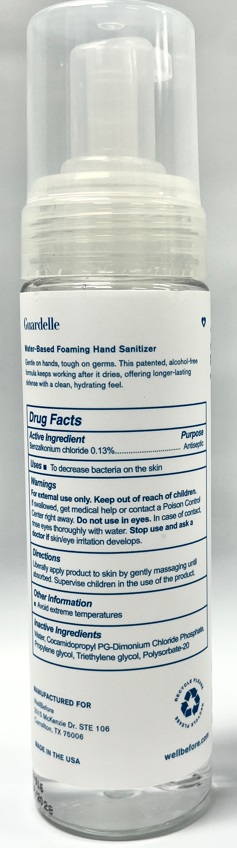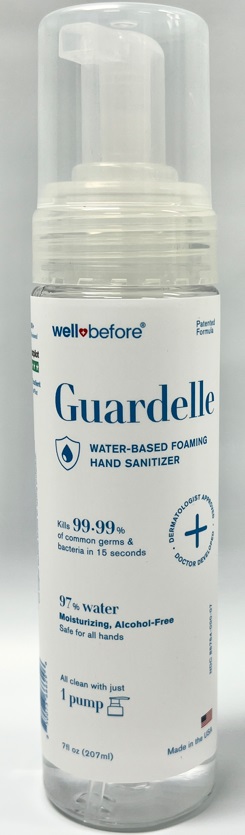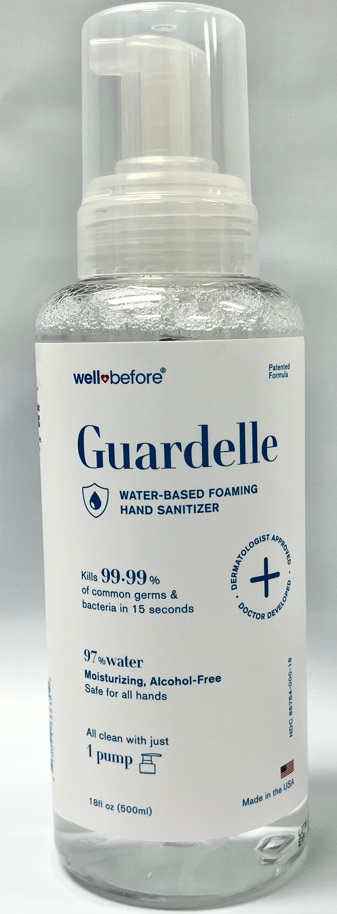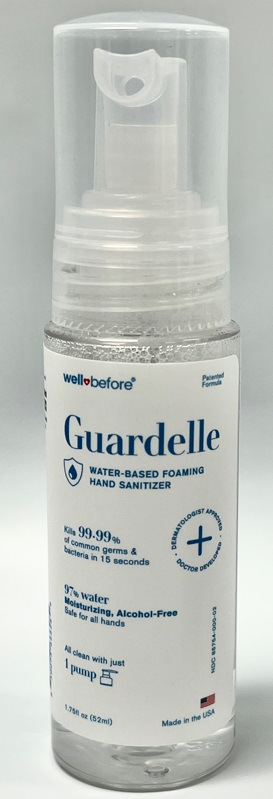 DRUG LABEL: Guardelle
NDC: 85754-000 | Form: AEROSOL, FOAM
Manufacturer: Social Medical Supply LLC
Category: otc | Type: HUMAN OTC DRUG LABEL
Date: 20251222

ACTIVE INGREDIENTS: BENZALKONIUM CHLORIDE 0.13 g/100 mL
INACTIVE INGREDIENTS: Water; COCAMIDOPROPYL PG-DIMONIUM CHLORIDE PHOSPHATE; PROPYLENE GLYCOL; TRIETHYLENE GLYCOL; POLYSORBATE 20

Guardelle Sanitizer Unscented

Active Ingredient

Benzalkonium chloride 0.13%

Purpose

Antiseptic

Uses

To decrease bacteria on the skin

Warnings

For external use only.

Keep out of reach of children.

If swallowed, get medical help or contact a Poison Control Center right away.

Do not use in eyes.

In case of contact, rinse eyes thoroughly with water.

Stop use and ask a doctor if

skin/eye irritation develops.

Directions

Liberally apply product to skin by gently massaging until

absorbed. Supervise children in the use of the product.

Other Information

• Avoid extreme temperatures.

Inactive Ingredients

Water, Cocamidolpropyl PG-Dimonium Chloride Phospate,

Propylene glycol, Triethylene glycol, Polysorbate-20

PACKAGE LABEL

Guardelle

WATER-BASED FOAMING
HAND SANITIZER

kills 99.9% of common germs &
bacteria in 15 seconds
97% water

Moisturizing, Alcohol-Free

Safe for all hands
All clean with just
1 pump

Manufactured for
WellBefore
2015 Mckenzie Dr. STE 106 Carrollton,
TX, 75006. Made in the USA wellbefore.com

1.7 OZ

7.0 OZ

18 OZ

res